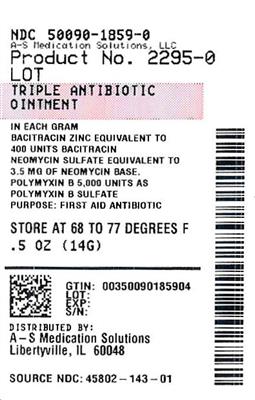 DRUG LABEL: TRIPLE ANTIBIOTIC
NDC: 50090-1859 | Form: OINTMENT
Manufacturer: A-S Medication Solutions
Category: otc | Type: HUMAN OTC DRUG LABEL
Date: 20241106

ACTIVE INGREDIENTS: BACITRACIN ZINC 400 [USP'U]/1 g; NEOMYCIN SULFATE 3.5 mg/1 g; POLYMYXIN B SULFATE 5000 [USP'U]/1 g
INACTIVE INGREDIENTS: PETROLATUM; COCOA BUTTER; COTTONSEED ACID; OLEA EUROPAEA (OLIVE) FRUIT OIL; SODIUM PYRUVATE; ALPHA-TOCOPHEROL ACETATE

TRIPLE ANTIBIOTIC

Active ingredients (in each gram)

Bacitracin zinc equivalent to 400 units bacitracin

Neomycin sulfate equivalent to 3.5 mg of neomycin base

Polymyxin B 5,000 units as polymyxin B sulfate

Purpose

First aid antibiotic

Use

first aid to help prevent infection in minor:

- cuts
- scrapes
- burns

Warnings

For external use only.

Do not use

- if you are allergic to any of the ingredients
- in the eyes
- over large areas of the body

Ask a doctor before use if you have

- deep or puncture wounds
- animal bites
- serious burns

Stop use and ask a doctor if

- you need to use longer than 1 week
- condition persists or gets worse
- rash or other allergic reaction develops

Keep out of reach of children.

If swallowed, get medical help or contact a Poison Control Center right away. (1-800-222-1222)

Directions

- clean the affected area
- apply a small amount of this product (an amount equal to the surface area of the tip of a finger) on the area 1 to 3 times daily
- may be covered with a sterile bandage

Other information

- store at 20-25°C (68-77°F)

Inactive ingredients

cocoa butter, cottonseed oil, olive oil, sodium pyruvate, tocopheryl acetate, white petrolatum

Questions or comments?

1-800-719-9260